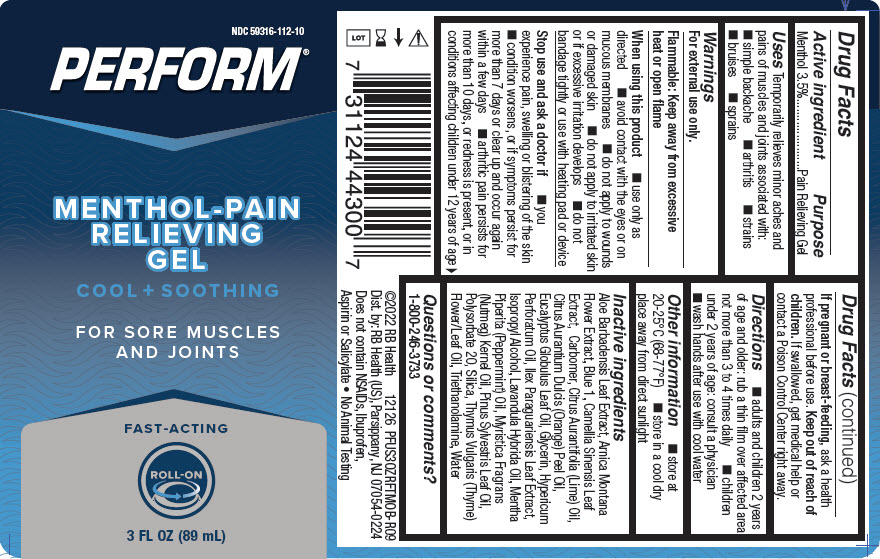 DRUG LABEL: PERFORM COOL AND SOOTHING PAIN RELIEVING ROLL-ON
NDC: 59316-112 | Form: GEL
Manufacturer: RB Health (US) LLC
Category: otc | Type: HUMAN OTC DRUG LABEL
Date: 20241227

ACTIVE INGREDIENTS: MENTHOL, UNSPECIFIED FORM 35 mg/1 mL
INACTIVE INGREDIENTS: ALOE VERA LEAF; ARNICA MONTANA FLOWER; FD&C BLUE NO. 1; GREEN TEA LEAF; LIME OIL, COLD PRESSED; ORANGE OIL, COLD PRESSED; EUCALYPTUS OIL; GLYCERIN; HYPERICUM OIL; ILEX PARAGUARIENSIS LEAF; ISOPROPYL ALCOHOL; LAVANDIN OIL; PEPPERMINT OIL; NUTMEG OIL; PINE NEEDLE OIL (PINUS SYLVESTRIS); POLYSORBATE 20; SILICON DIOXIDE; THYME OIL; TROLAMINE; WATER

PERFORM COOL AND SOOTHING PAIN RELIEVING ROLL-ON

Active Ingredients

Menthol 3.5%

Purpose

Pain Relieving Gel

Uses:

Temporarily relieves minor aches and pains of muscles and joints associated with:

- simple backache
- arthritis
- strains
- bruises
- sprains

Warnings

For external use only.

Flammable:

Keep away from excessive heat and open flame.

When Using This Product:

- use only as directed
- Avoid contact with the eyes or mucous membranes
- do not apply to wounds or damaged skin
- do not apply to irritated skin or if excessive irritation develops
- do not bandage tightly or use with heating pad or device

Stop Use and Ask Doctor If:

- you experience pain, swelling or blistering of the skin
- condition worsens, or if symptoms persist for more than 7 days or clear up and occur again within a few days
- arthritic pain persists for more than 10 days, or redness is present, or in conditions affecting children under 12 years of age

PREGNANCY OR BREAST FEEDING

If pregnant or breast-feeding,ask a health professional before use.

Keep out of reach of children.If swallowed, get medical help or contact a Poison Control Center right away.

Directions:

- adults and children 2 years of age and older: rub a thin film over affected area not more than 3 to 4 times daily
- children under 2 years of age: consult a physician
- wash hands after use with cool water

Other Information:

- store at 20-25C (68-77F)
- store in a cool dry place away from direct sunlight

Inactive Ingredients:

Aloe Barbadensis Leaf Extract, Arnica Montana Flower Extract, Blue 1, Camelia Sinensis Leaf Extract, Carbomer, Citrus Aurantifolia (lime) Oil, Citrus Auratium Dulcis (Orange) Peel Oil, Eucalyptus Globulus Leaf Oil, Glycerin, Hypericum Perforatum Oil, Ilex Paraguariensis Leaf Extract, Isopropyl Alcohol, Lavandula Hybrida Oil, Mentha Piperita (Peppermint) Oil, Myristica Fragrans (Nutmeg) Kerneol Oil, Pinus Sylvestris Leaf Oil, Polysorbate 20, Silica, Thymus Vulgaris (Thyme) Flower/Leaf Oil, Triethanolamine, Water.

Questions or Comments?

1-800-246-3733

PRINCIPAL DISPLAY PANEL - 89 mL Bottle Label

NDC 59316-112-10

PERFORM®

MENTHOL-PAIN
RELIEVING
GEL
COOL + SOOTHING
FOR SORE MUSCLES
AND JOINTS

FAST-ACTING

ROLL-ON

3 FL OZ (89 mL)